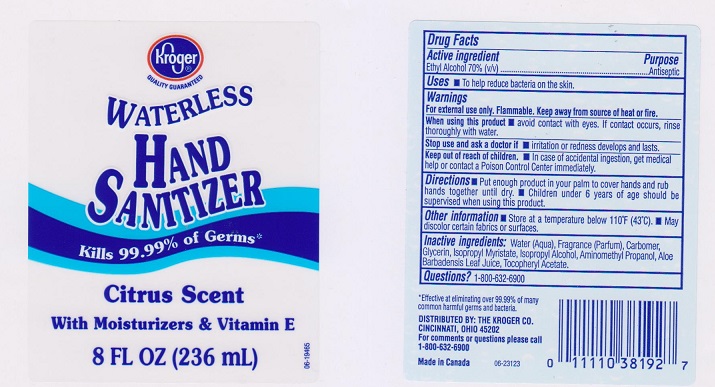 DRUG LABEL: Kroger
NDC: 30142-405 | Form: LIQUID
Manufacturer: The Kroger Company
Category: otc | Type: HUMAN OTC DRUG LABEL
Date: 20170425

ACTIVE INGREDIENTS: ALCOHOL 700 mg/1 mL
INACTIVE INGREDIENTS: WATER; CARBOMER 934; GLYCERIN; ISOPROPYL MYRISTATE; ISOPROPYL ALCOHOL; AMINOMETHYLPROPANOL; ALOE VERA LEAF; .ALPHA.-TOCOPHEROL ACETATE, DL-

Drug Facts

Active ingredient

Ethyl Alcohol 70% (v/v)

Purpose

Antiseptic

Uses

- To help reduce bacteria on the skin.

Warnings

For external use only. Flammable. Keep away from source of heat or fire.

When using this product

- Avoid contact with eyes. If contact occurs, rinse thoroughly with water.

Stop use and ask a doctor if

- irritation or redness develops and lasts.

Keep out of reach of children.

- In case of accidental ingestion, get medical help or contact a Poison Control Center immediately.

Directions

- Put enough product in your palm to cover hands and rub hands together until dry.
- Children under 6 years of age should be supervised when using this product.

Other information

- Store at a temperature below 110°F (43°C).
- May discolor certain fabrics or surfaces.

Inactive ingredients

Water (Aqua), Fragrance (Parfum), Carbomer, Glycerin, Isopropyl Myristate, Isopropyl Alcohol, Aminomethyl Propanol, Aloe Barbadensis Leaf Juice, Tocopheryl Acetate.

Questons?

1-800-632-6900